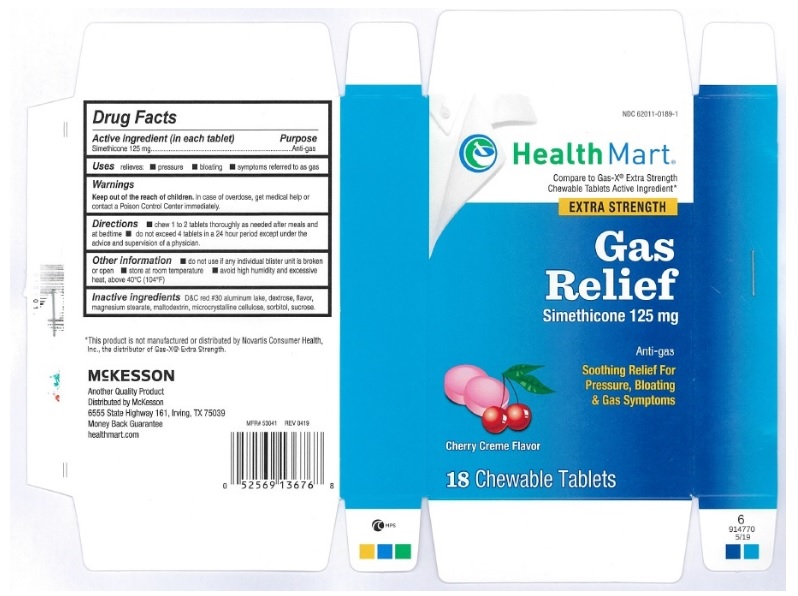 DRUG LABEL: gas relief
                
NDC: 62011-0189 | Form: TABLET, CHEWABLE
Manufacturer: Strategic Sourcing Services LLC
Category: otc | Type: HUMAN OTC DRUG LABEL
Date: 20250103

ACTIVE INGREDIENTS: DIMETHICONE 125 mg/1 1
INACTIVE INGREDIENTS: D&C RED NO. 30; DEXTROSE; MAGNESIUM STEARATE; MALTODEXTRIN; CELLULOSE, MICROCRYSTALLINE; SORBITOL; SUCROSE

gas relief

Active ingredient (in each tablet)

simethicone 125 mg

Purpose

Anti-gas

Uses

relieves:

- pressure
- bloating
- symptoms referred to as gas

Warnings

Keep out of the reach of children. In case of overdose, get medical help or contact a Poison Control Center immediately.

Directions

- chew 1 to 2 tablets thoroughly as needed after meals and at bedtime
- do not exceed 4 tablets in a 24 hour period except under the advice and supervision of a physician

Other information

- do not use if any individual blister unit is broken or open
- store at room temperature
- avoid high humidity and excessive heat, above 40oC (104oF)

Inactive ingredients

D&C red 30 aluminum lake, dextrose, flavor, magnesium stearate, maltodextrin, microcrystalline cellulose, sorbitol, sucrose

Principal Display Panel

NDC 62011-0189-1

HealthMart

Compare to Gas-X® Extra strength Chewable Tablets Active Ingredient*

EXTRA STRENGTH

Gas Relief

Simethicone 125 mg

Anti-gas

Soothing Relief For Pressure, Bloating & Gas Symptoms

Cherry Creme Flavor

18 Chewable Tablets